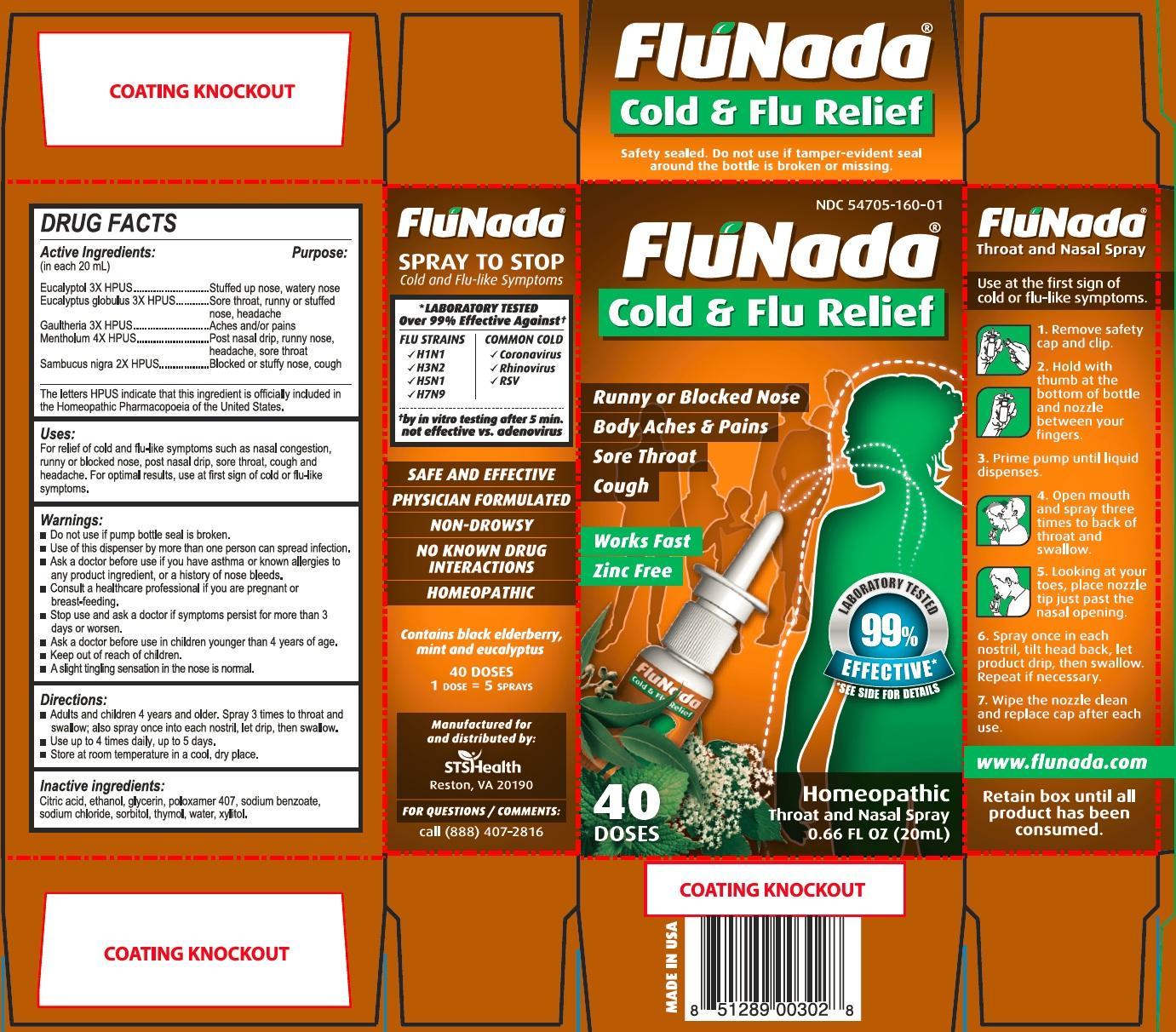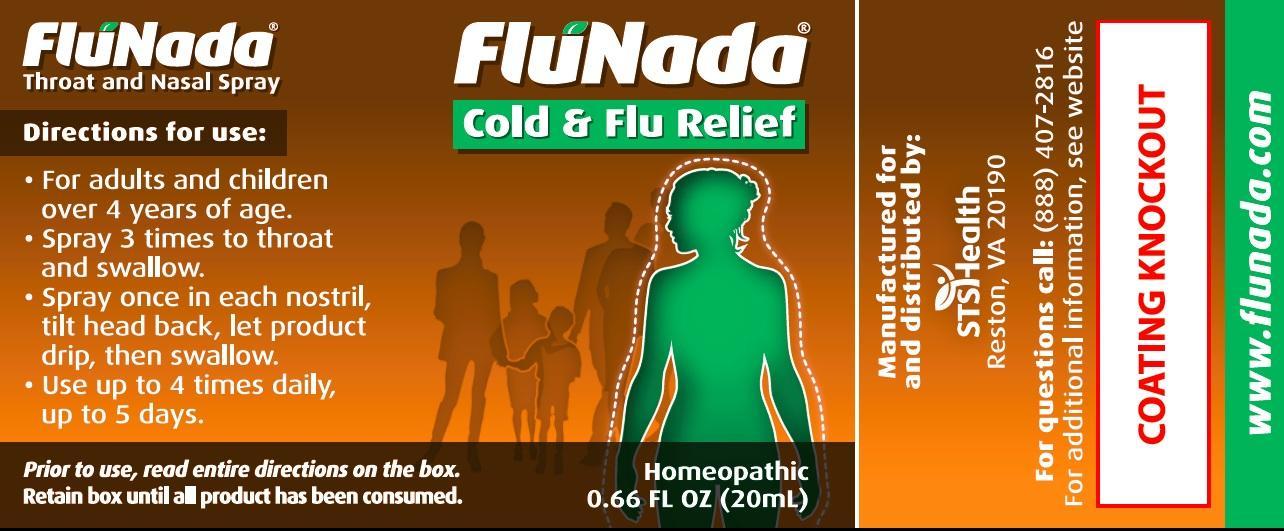 DRUG LABEL: FluNada
NDC: 54705-160 | Form: SPRAY, METERED
Manufacturer: Flutrends International Corporation
Category: homeopathic | Type: HUMAN OTC DRUG LABEL
Date: 20191216

ACTIVE INGREDIENTS: EUCALYPTOL 3 [hp_X]/20 mL; EUCALYPTUS GLOBULUS WHOLE 3 [hp_X]/20 mL; MENTHOL 4 [hp_X]/20 mL; SAMBUCUS NIGRA WHOLE 2 [hp_X]/20 mL; METHYL SALICYLATE 3 [hp_X]/20 mL
INACTIVE INGREDIENTS: WATER; ALCOHOL; XYLITOL; POLOXAMER 407; GLYCERIN; SORBITOL; SODIUM CHLORIDE; CITRIC ACID MONOHYDRATE; SODIUM BENZOATE; THYMOL

FluNada Cold and Flu Relief - Drug Facts Label

Active Ingredients: (in each 20 mL)

Eucalyptol 3x HPUS

Eucalyptus globulus 3x HPUS

Gaultheria 3x HPUS

Mentholum 4x HPUS

Sambucus nigra 2x HPUS

Purpose

- Stuffed up nose, watery nose
- Sore throat, runny or stuffed nose, headache
- Aches and/or pains
- Post nasal drip, runny nose, headache, sore throat
- Blocked or stuffy nose, cough

DESCRIPTION

The letters HPUS indicate that this ingredient is officially included in the Homeopathic Pharmacopoeia of the United States.

Uses:

For relief of cold and flu-like symptoms such as nasal congestion, runny or blocked nose, post nasal drip, sore throat, cough and headache. For optimal results, use at first sign of cold or flu-like symptoms.

Warnings:

- Do not use if pump bottle seal is broken.
- Use of this dispenser by more than one person can spread infection.
- Ask a doctor before use if you have asthma or known allergies to any product ingredient, or a history of nose bleeds.
- Consult a healthcare professional if you are pregnant or breast-feeding.
- Stop use and ask a doctor if symptoms persist for more than 3 days or worsen.
- Ask a doctor before use in children younger than 4 years of age.
- Keep out of reach of children.

Directions:

- Adults and children 4 years and older. Spray 3 times to throat and swallow; also spray once into each nostril, let drip, then swallow.
- Use up to 4 times daily, up to 5 days.
- Store at room temperature in a cool, dry place.

Inactive Ingredients:

Citric acid, ethanol, glycerin, poloxamer 407, sodium benzoate, sodium chloride, sorbitol, thymol, water, xylitol.

FOR QUESTIONS / COMMENTS:

call (888) 407-2816

www.flunada.com

Image of 20mL Carton and Label

FluNadaCarton2014.jpg FluNadaLabel2014.jpg